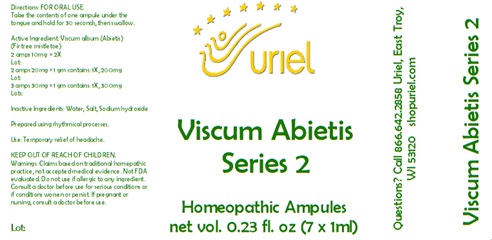 DRUG LABEL: Viscum Abietis Series 2 7ml
NDC: 48951-9264 | Form: LIQUID
Manufacturer: Uriel Pharmacy Inc.
Category: homeopathic | Type: HUMAN OTC DRUG LABEL
Date: 20241204

ACTIVE INGREDIENTS: VISCUM ALBUM FRUITING TOP 1 [hp_X]/1 mL
INACTIVE INGREDIENTS: SODIUM CHLORIDE; WATER; SODIUM HYDROXIDE

Viscum Abietis Series 2 7ml

INDICATIONS AND USAGE

Directions: FOR ORAL USE.

DOSAGE AND ADMINISTRATION

Take the contents of one ampule under the tongue and hold for 30 seconds, then swallow.

Active Ingredient: Viscum Abietis (Fir tree mistletoe)

2 amps 10mg = 2X

2 amps 20mg = 1 gm contains: 1X, 200mg
3 amps 30mg = 1 gm contains: 1X, 300mg

Inactive Ingredients: Water, Salt, Sodium hydroxide

Prepared using rhythmical processes.

PURPOSE

Use: Temporary relief of headache.

KEEP OUT OF REACH OF CHILDREN.

WARNINGS

Warnings: Claims based on traditional homepathic practice, not accepted medical evidence. Not FDA evaluated. Do not use if allergic to any ingredient. Consult a doctor before use for serious conditions or if conditions worsen or persist. If pregnant or nursing, consult a doctor before use.

QUESTIONS

Questions? Call 866.642.2858 Uriel, East Troy, WI 53120 shopuriel.com